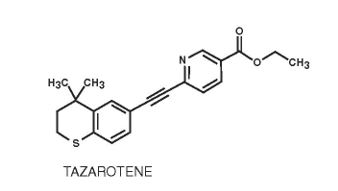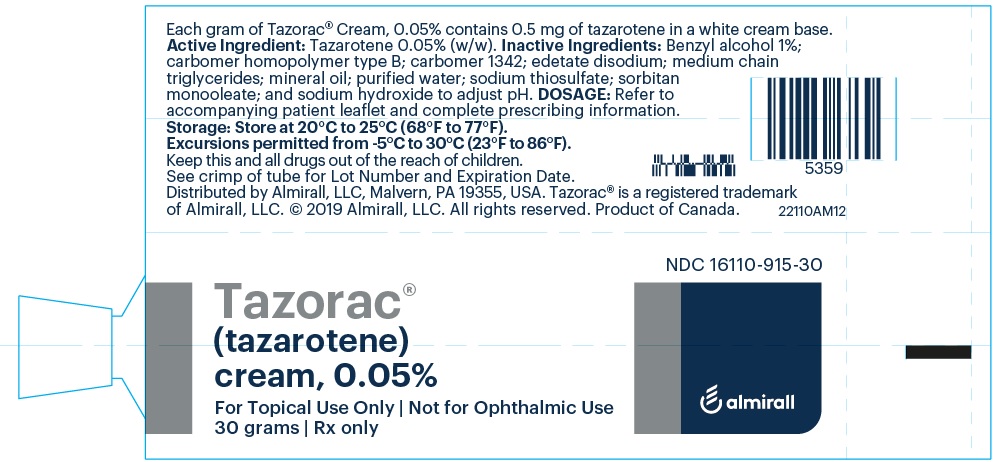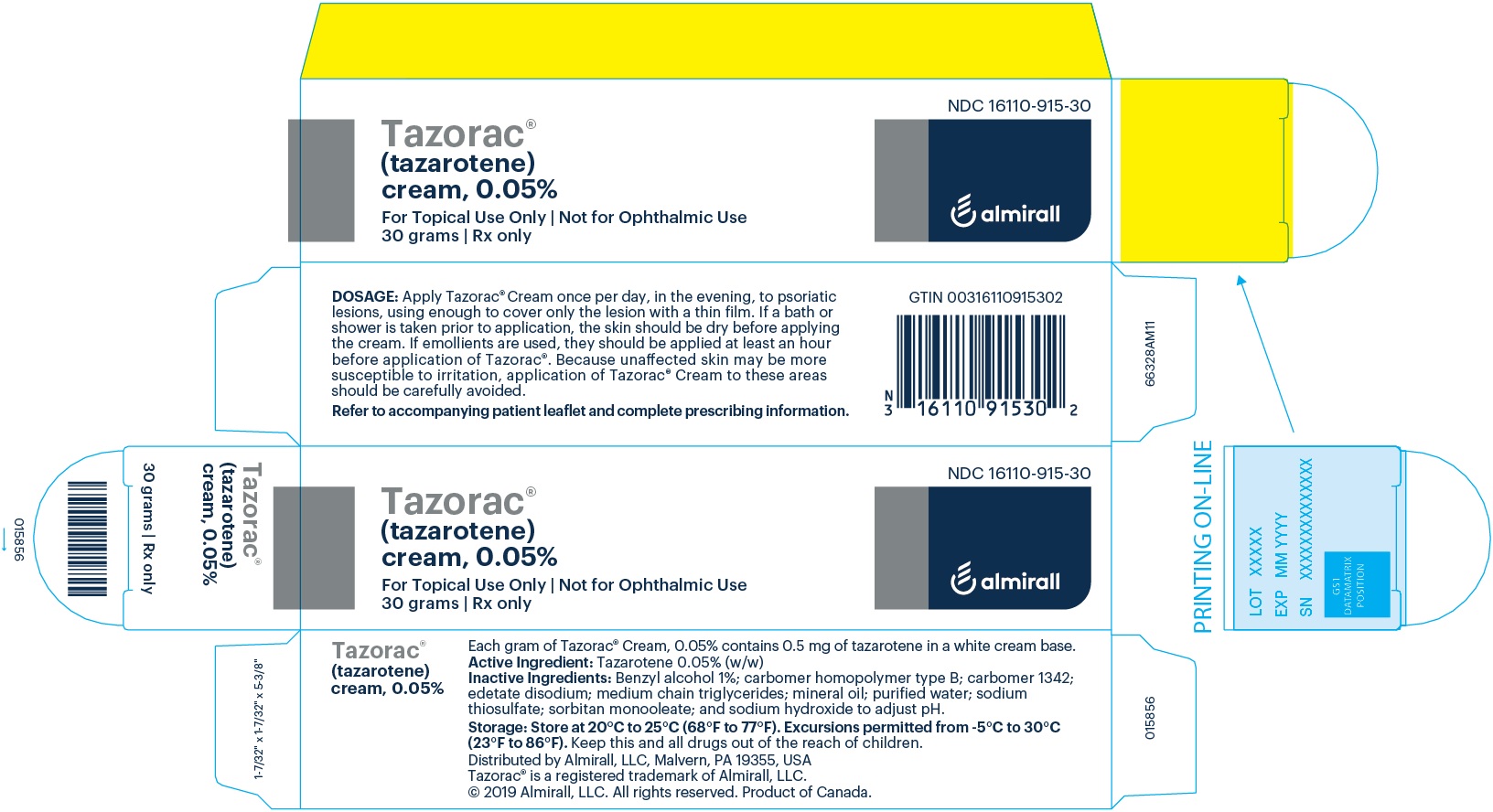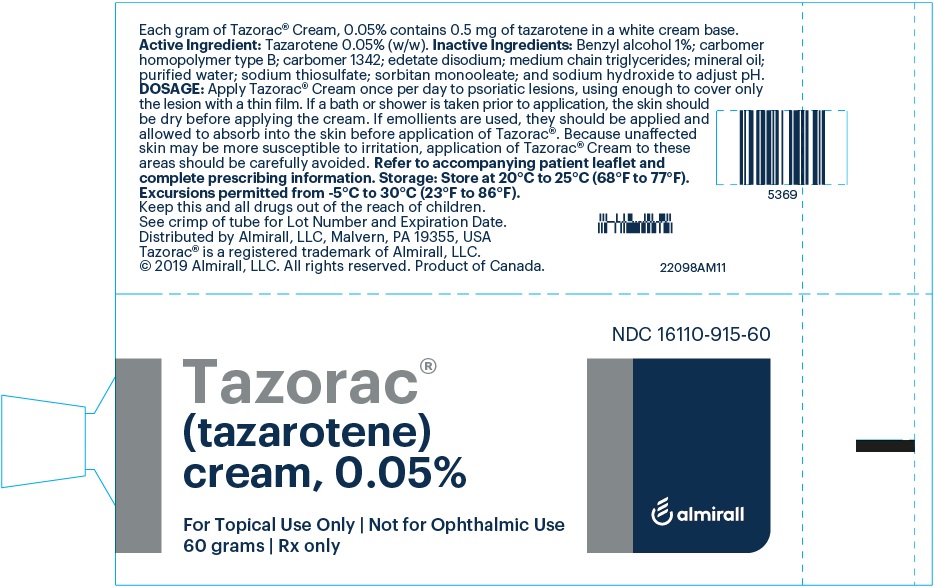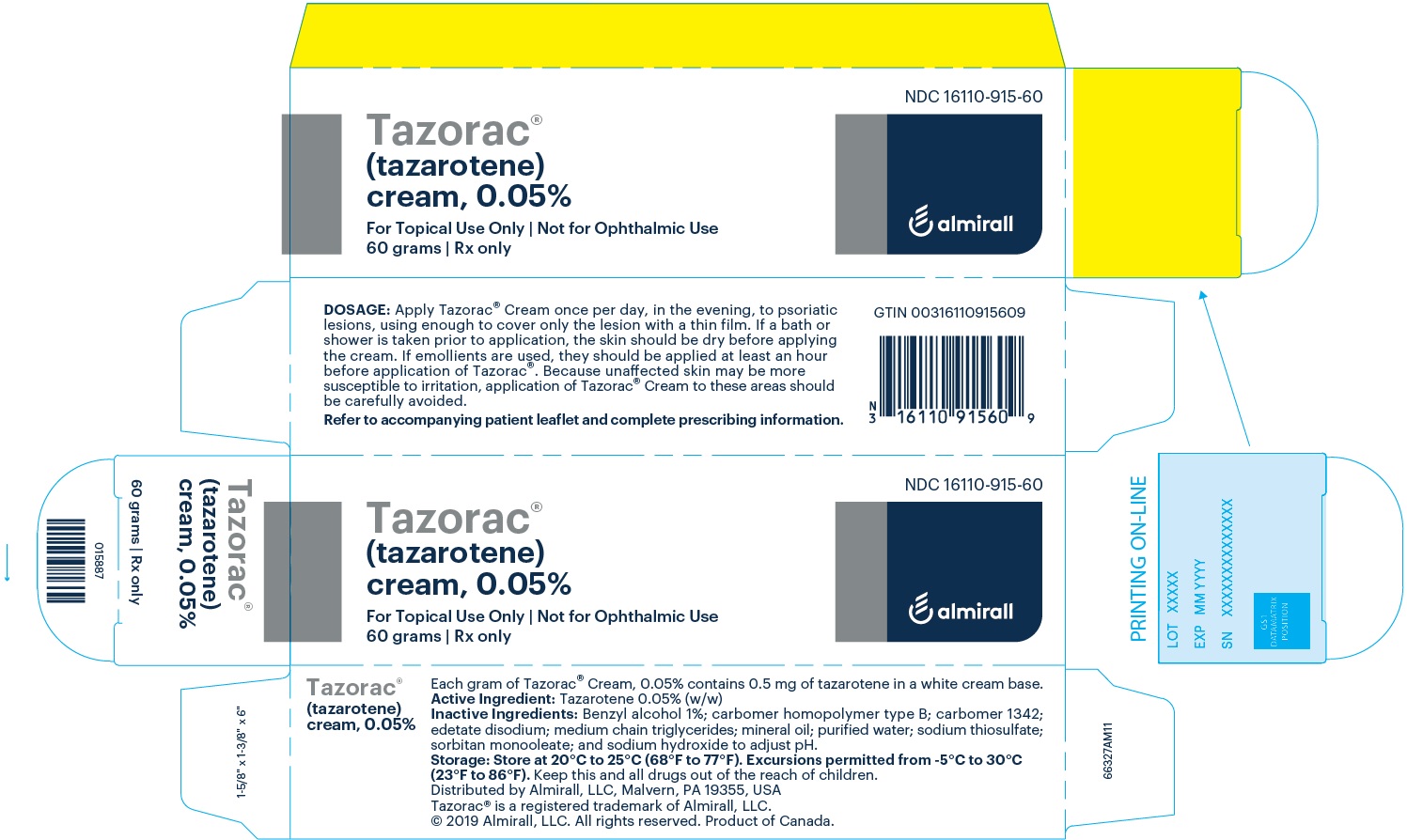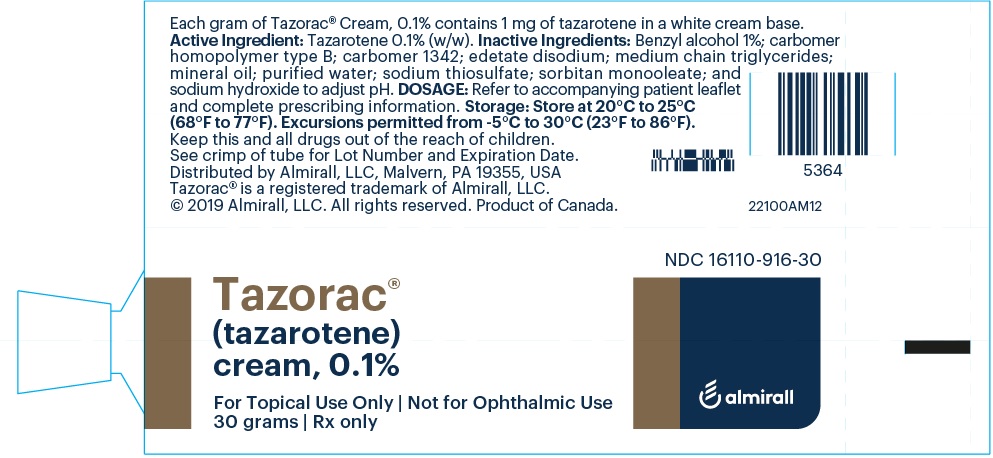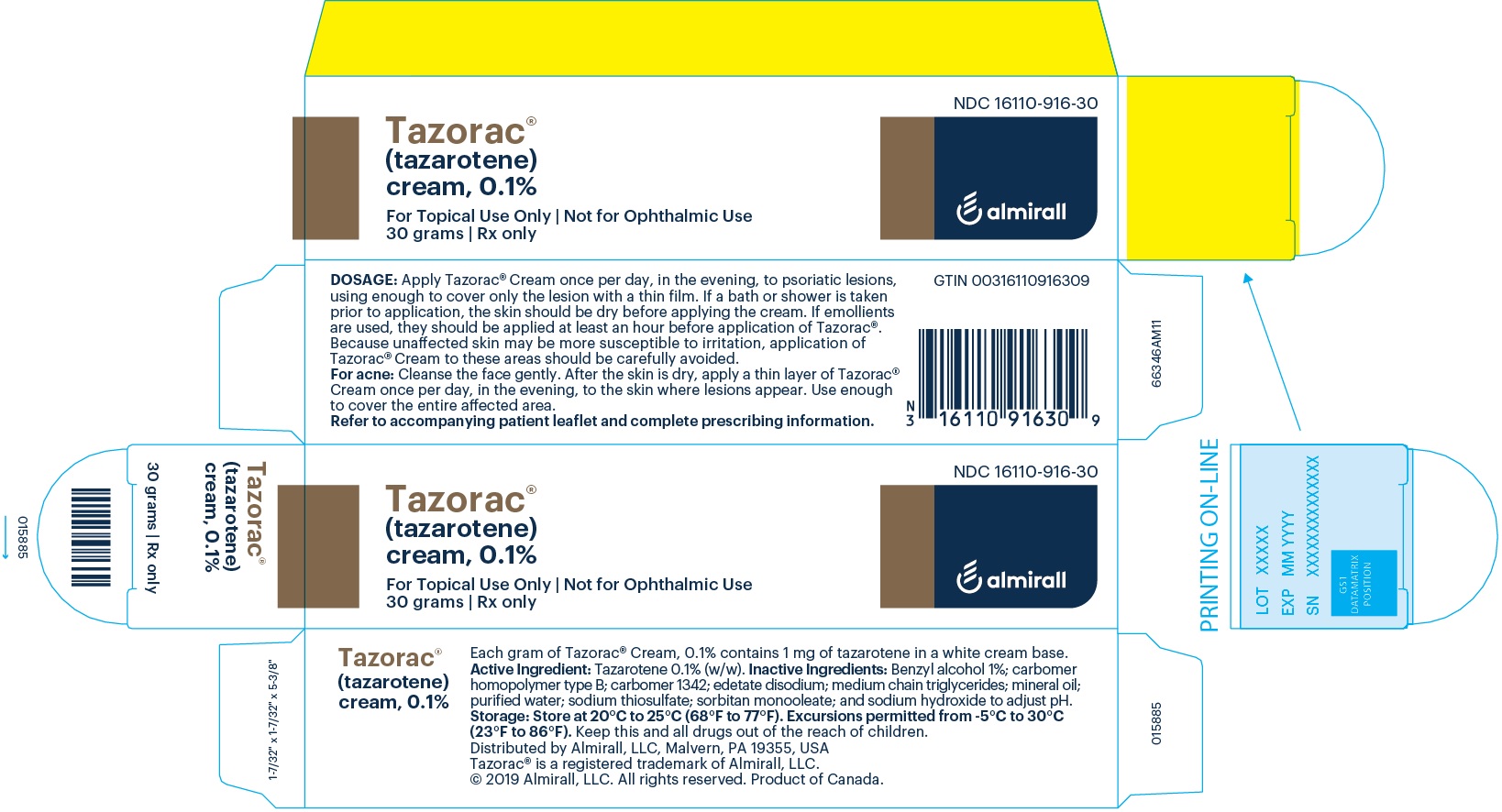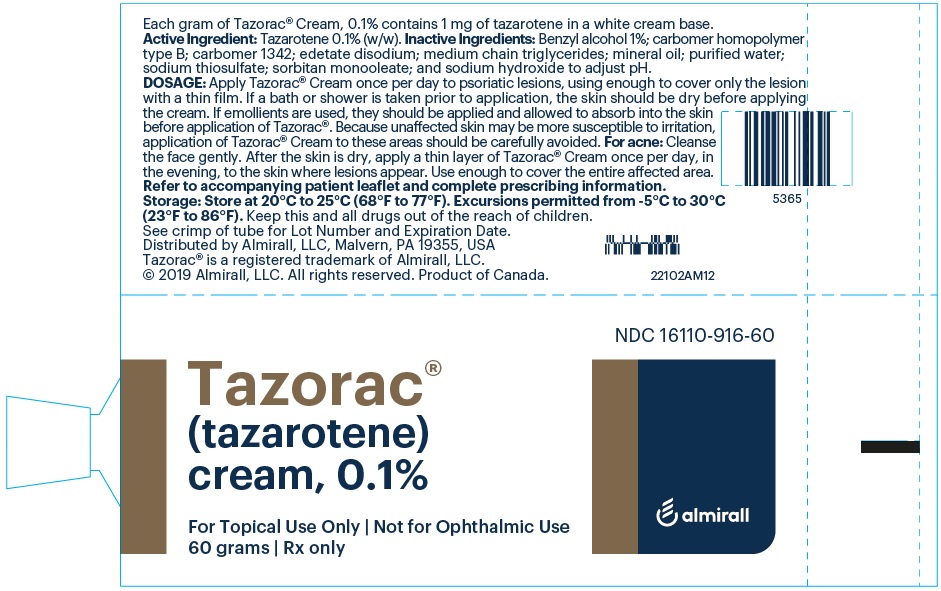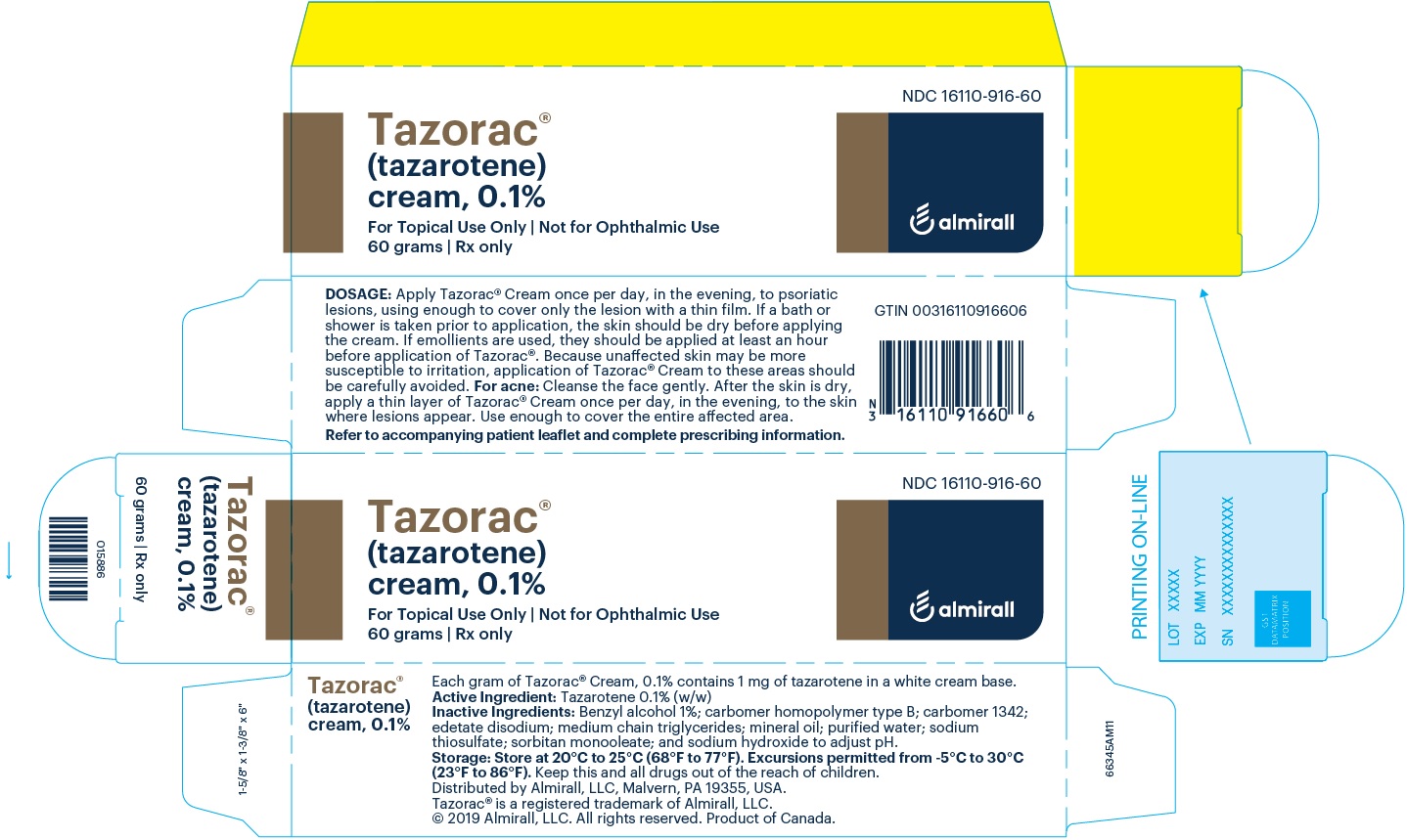 DRUG LABEL: TAZORAC
NDC: 16110-915 | Form: CREAM
Manufacturer: Almirall, LLC
Category: prescription | Type: HUMAN PRESCRIPTION DRUG LABEL
Date: 20251113

ACTIVE INGREDIENTS: tazarotene 0.05 mg/1 g
INACTIVE INGREDIENTS: Benzyl alcohol; CARBOMER HOMOPOLYMER TYPE B (ALLYL PENTAERYTHRITOL CROSSLINKED); carbomer 1342; edetate disodium; GLYCERYL MONO- AND DICAPRYLOCAPRATE; mineral oil; water; sodium thiosulfate; sorbitan monooleate; sodium hydroxide

HIGHLIGHTS OF PRESCRIBING INFORMATION

These highlights do not include all the information needed to use TAZORAC® Cream safely and effectively. See full prescribing information for TAZORAC® Cream.
TAZORAC® (tazarotene) cream, 0.05% and 0.1%, for topical use
Initial U.S. Approval: 1997

1 INDICATIONS AND USAGE

- TAZORAC® Cream 0.05% and 0.1% is a retinoid indicated for the topical treatment of plaque psoriasis. (1.1)
- TAZORAC Cream 0.1% is indicated for the topical treatment of acne vulgaris. (1.2)

2 DOSAGE AND ADMINISTRATION

- Apply a thin layer of TAZORAC Cream only to the affected area once daily in the evening. (2.1, 2.2)
- Not for ophthalmic, oral, or intravaginal use. (2.2)
- If contact with eyes occurs, rinse thoroughly with water. (2.2)

3 DOSAGE FORMS AND STRENGTHS

Cream, 0.05% and 0.1%. (3)

4 CONTRAINDICATIONS

- Pregnancy (4, 8.1)
- Hypersensitivity (4)

5 WARNINGS AND PRECAUTIONS

- Embryofetal Toxicity: TAZORAC Cream contains tazarotene, which is a teratogenic substance. TAZORAC Cream is contraindicated in pregnancy. Females of child-bearing potential should have a negative pregnancy test within 2 weeks prior to initiating treatment and use an effective method of contraception during treatment. (5.1)
- Local Irritation: Some individuals may experience excessive pruritus, burning, skin redness or peeling. If these effects occur, discontinue until the integrity of the skin has been restored, or reduce dosing interval, or in the case of psoriasis, may switch to the lower concentration. TAZORAC Cream should not be used on eczematous skin, as it may cause severe irritation. (5.2)
- Photosensitivity and Risk for Sunburn: Avoid exposure to sunlight, sunlamps, and weather extremes. Wear sunscreen daily. TAZORAC Cream should be administered with caution if the patient is also taking drugs known to be photosensitizers. (5.3)

6 ADVERSE REACTIONS

- Plaque psoriasis: Most common adverse reactions occurring in 10 to 23% of patients are pruritus, erythema, and burning. (6.1)
- Acne Vulgaris: Most common adverse reactions occurring in 10 to 30% of patients are desquamation, dry skin, erythema, and burning sensation. (6.1)

To report SUSPECTED ADVERSE REACTIONS, contact Allergan at 1-800-678-1605 or FDA at 1-800-FDA-1088 or www.fda.gov/medwatch.

FULL PRESCRIBING INFORMATION

1 INDICATIONS AND USAGE

1.1 Plaque Psoriasis

TAZORAC® (tazarotene) Cream, 0.05% and 0.1% are indicated for the topical treatment of patients with plaque psoriasis.

1.2 Acne Vulgaris

TAZORAC (tazarotene) Cream, 0.1% is also indicated for the topical treatment of patients with acne vulgaris.

2 DOSAGE AND ADMINISTRATION

2.1 Important Administration Instructions

TAZORAC Cream is for topical use only. TAZORAC Cream is not for ophthalmic, oral, or intravaginal use. If contact with mucous membranes occurs, rinse thoroughly with water [see Warnings and Precaution (5.2)].

Wash hands thoroughly after application.

2.2 Psoriasis

It is recommended that treatment starts with TAZORAC Cream, 0.05%, with strength increased to 0.1% if tolerated and medically indicated. Apply a thin film (2 mg/cm^2) of TAZORAC Cream once per day, in the evening, to cover only the psoriatic lesions. If a bath or shower is taken prior to application, the skin should be dry before applying the cream. If emollients are used, they should be applied at least an hour before application of TAZORAC Cream. Because unaffected skin may be more susceptible to irritation, application of TAZORAC Cream to these areas should be carefully avoided.

2.3 Acne

Cleanse the face gently. After the skin is dry, apply a thin layer (2 mg/cm^2) of TAZORAC Cream 0.1% once per day, in the evening, to the skin areas where acne lesions appear. Use enough to cover the entire affected area.

Use effective sunscreens and wear protective clothing while using TAZORAC Cream [see Warnings and Precaution (5.3)].

3 DOSAGE FORMS AND STRENGTHS

Cream, 0.05% and 0.1%. Each gram of TAZORAC Cream, 0.05% and 0.1% contains 0.5 mg and 1 mg of tazarotene, respectively in a white cream base.

4 CONTRAINDICATIONS

TAZORAC Cream is contraindicated in:

- Pregnancy. Retinoids may cause fetal harm when administered to a pregnant female [see Warnings and Precautions (5.1), Use in Specific Populations (8.1, 8.3)].
- Individuals who have known hypersensitivity to any of its components [see Warnings and Precautions (5.2)].

5 WARNINGS AND PRECAUTIONS

5.1 Embryofetal Toxicity

Systemic exposure to tazarotenic acid is dependent upon the extent of the body surface area treated. In patients treated topically over sufficient body surface area, exposure could be in the same order of magnitude as in orally treated animals. Although there may be less systemic exposure in the treatment of acne of the face alone due to less surface area for application, tazarotene is a teratogenic substance, and it is not known what level of exposure is required for teratogenicity in humans [see Clinical Pharmacology (12.3)].

There were thirteen reported pregnancies in subjects who participated in the clinical trials for topical tazarotene. Nine of the subjects were found to have been treated with topical tazarotene, and the other four had been treated with vehicle. One of the subjects who was treated with tazarotene cream elected to terminate the pregnancy for non-medical reasons unrelated to treatment. The other eight pregnant women who were inadvertently exposed to topical tazarotene during clinical trials subsequently delivered apparently healthy babies. As the exact timing and extent of exposure in relation to the gestation times are not certain, the significance of these findings is unknown.

Females of Child-bearing Potential

Females of child-bearing potential should be warned of the potential risk and use adequate birth-control measures when TAZORAC Cream is used. The possibility that a female of child-bearing potential is pregnant at the time of institution of therapy should be considered.

A negative result for pregnancy test should be obtained within 2 weeks prior to TAZORAC Cream therapy. TAZORAC Cream therapy should begin during a menstrual period [see Use in Specific Populations (8.1)].

5.2 Local Irritation and Hypersensitivity Reactions

Local tolerability reactions (including blistering and skin desquamation) and hypersensitivity adverse reactions (including urticaria) have been observed with topical tazarotene. Application of TAZORAC Cream may cause excessive irritation in the skin of certain sensitive individuals. Some individuals may experience excessive pruritus, burning, skin redness or peeling. If these effects occur, the medication should either be discontinued until the integrity of the skin is restored, or the dosing should be reduced to an interval the patient can tolerate. However, efficacy at reduced frequency of application has not been established. Alternatively, patients with psoriasis who are being treated with the 0.1% concentration can be switched to the lower concentration. Frequency of application should be closely monitored by careful observation of the clinical therapeutic response and skin tolerance. Therapy can be resumed, or the drug concentration or frequency of application can be increased as the patient becomes able to tolerate treatment.

Concomitant topical medications and cosmetics that have a strong drying effect should be avoided. It is also advisable to "rest" a patient's skin until the effects of such preparations subside before use of TAZORAC Cream is begun.

TAZORAC Cream, should not be used on eczematous skin, as it may cause severe irritation.

Weather extremes, such as wind or cold, may be more irritating to patients using TAZORAC Cream.

5.3 Photosensitivity and Risk for Sunburn

Because of heightened burning susceptibility, exposure to sunlight (including sunlamps) should be avoided unless deemed medically necessary, and in such cases, exposure should be minimized during the use of TAZORAC Cream. Patients must be warned to use sunscreens and protective clothing when using TAZORAC Cream. Patients with sunburn should be advised not to use TAZORAC Cream until fully recovered. Patients who may have considerable sun exposure due to their occupation and those patients with inherent sensitivity to sunlight should exercise particular caution when using TAZORAC Cream.

TAZORAC Cream should be administered with caution if the patient is also taking drugs known to be photosensitizers (e.g., thiazides, tetracyclines, fluoroquinolones, phenothiazines, sulfonamides) because of the increased possibility of augmented photosensitivity.

6 ADVERSE REACTIONS

The following serious adverse reactions are discussed in more detail in other sections of the labeling:

- Embryofetal toxicity [see Warnings and Precautions (5.1)]
- Photosensitivity and Risk of Sunburn [see Warnings and Precautions (5.3)]

6.1 Clinical Trials Experience

Because clinical trials are conducted under widely varying conditions, adverse reaction rates observed in the clinical trials of a drug cannot be directly compared to rates in the clinical trials of another drug and may not reflect the rates observed in clinical practice.

In human dermal safety trials, TAZORAC Cream, 0.05% and 0.1% did not induce allergic contact sensitization, phototoxicity, or photoallergy.

Psoriasis

The most frequent adverse reactions reported with TAZORAC Cream, 0.05% and 0.1% occurring in 10 to 23% of subjects, in descending order, included pruritus, erythema, and burning. Reactions occurring in greater than 1 to less than 10% of subjects, in descending order, included irritation, desquamation, stinging, contact dermatitis, dermatitis, eczema, worsening of psoriasis, skin pain, rash, hypertriglyceridemia, dry skin, skin inflammation, and peripheral edema.

TAZORAC Cream, 0.1% was associated with a greater degree of local irritation than the 0.05% cream. The rates of irritation adverse reactions reported during psoriasis trials with TAZORAC Cream, 0.1% were 0.1-0.4% higher than those reported for TAZORAC Cream, 0.05%.

Acne

The most frequent adverse reactions reported during clinical trials with TAZORAC Cream 0.1% in the treatment of acne, occurring in 10-30% of subjects, in descending order included desquamation, dry skin, erythema, and burning sensation. Reactions occurring in 1 to 5% of subjects included pruritus, irritation, face pain, and stinging.

6.2 Postmarketing Experience

The following adverse reactions have been identified during postapproval use of tazarotene. Because these reactions are reported voluntarily from a population of uncertain size, it is not always possible to reliably estimate their frequency or establish a causal relationship to drug exposure.

Skin and subcutaneous tissue disorders: blister, dermatitis, urticaria, skin exfoliation, skin discoloration (including skin hyperpigmentation or skin hypopigmentation), swelling at or near application sites, and pain.

7 DRUG INTERACTIONS

No formal drug-drug interaction studies were conducted with TAZORAC Cream.

In a trial of 27 healthy female subjects between the ages of 20–55 years receiving a combination oral contraceptive tablet containing 1 mg norethindrone and 35 mcg ethinyl estradiol, concomitant use of tazarotene administered as 1.1 mg orally (mean ± SD Cmax and AUC0-24 of tazarotenic acid were 28.9 ± 9.4 ng/mL and 120.6 ± 28.5 ng•hr/mL) did not affect the pharmacokinetics of norethindrone and ethinyl estradiol over a complete cycle.

The impact of tazarotene on the pharmacokinetics of progestin only oral contraceptives (i.e., minipills) has not been evaluated.

8 USE IN SPECIFIC POPULATIONS

8.1 Pregnancy

Risk Summary

Based on data from animal reproduction studies, retinoid pharmacology, and the potential for systemic absorption, TAZORAC Cream may cause fetal harm when administered to a pregnant female and is contraindicated during pregnancy. Safety in pregnant females has not been established. The potential risk to the fetus outweighs the potential benefit to the mother from TAZORAC Cream during pregnancy; therefore, TAZORAC Cream should be discontinued as soon as pregnancy is recognized [see Contraindications (4), Warnings and Precautions (5.1), Clinical Pharmacology (12.3)]. Limited case reports of pregnancy in females enrolled in clinical trials for TAZORAC Cream have not established a clear association with tazarotene and major birth defects or miscarriage risk. Because the exact timing and extent of exposure in relation to the gestational age are not certain, the significance of these findings is unknown.

In animal reproduction studies with pregnant rats, tazarotene dosed topically during organogenesis at 2 times the maximum systemic exposure in subjects treated with the maximum recommended human dose (MRHD) of tazarotene cream, 0.1% resulted in reduced fetal body weights and reduced skeletal ossification. In animal reproduction studies with pregnant rabbits dosed topically with tazarotene gel at 26 times the maximum systemic exposure in subjects treated with the MRHD of tazarotene cream, 0.1%, there was a single incident of known retinoid malformations, including spina bifida, hydrocephaly, and heart anomalies.

In animal reproduction studies with pregnant rats and rabbits, tazarotene dosed orally during organogenesis at 2 and 52 times, respectively, the maximum systemic exposure in subjects treated with the MRHD of tazarotene cream, 0.1% resulted in malformations, fetal toxicity, developmental delays, and/or behavioral delays. In pregnant rats, tazarotene dosed orally prior to mating through early gestation resulted in decreased litter size, decreased numbers of live fetuses, decreased fetal body weights, and increased malformations at doses approximately 7 times higher than the maximum systemic exposure in subjects treated with the MRHD of tazarotene cream, 0.1% [see Data].

The background risk of major birth defects and miscarriage for the indicated population is unknown. Adverse outcomes in pregnancy occur regardless of the health of the mother or the use of medications. In the U.S. general population, the estimated background risk of major birth defects and miscarriage in clinically recognized pregnancies is 2-4% and 15-20%, respectively.

Data

Animal Data

In rats, a tazarotene gel, 0.05% formulation dosed topically during gestation days 6 through 17 at 0.25 mg/kg/day, which represented 2 times the maximum systemic exposure in subjects treated with the MRHD of tazarotene cream, 0.1% (i.e., 2 mg/cm^2 over a 15% body surface area), resulted in reduced fetal body weights and reduced skeletal ossification. Rabbits dosed topically with 0.25 mg/kg/day tazarotene gel, which represented 26 times the maximum systemic exposure in subjects treated with MRHD of tazarotene cream, 0.1%, during gestation days 6 through 18, had a single incident of known retinoid malformations, including spina bifida, hydrocephaly, and heart anomalies.

When tazarotene was given orally to animals, developmental delays were seen in rats, and malformations and post-implantation loss were observed in rats and rabbits at doses representing 2 and 52 times, respectively, the maximum systemic exposure seen in subjects treated with the MRHD of tazarotene cream, 0.1%.

In female rats orally administered 2 mg/kg/day of tazarotene from 15 days before mating through gestation day 7, which represented 7 times the maximum systemic exposure in subjects treated with the MRHD of tazarotene cream, 0.1%, classic developmental effects of retinoids were observed including decreased number of implantation sites, decreased litter size, decreased numbers of live fetuses, and decreased fetal body weights. A low incidence of retinoid-related malformations was observed at that dose.

In a pre- and postnatal development toxicity study, topical administration of tazarotene gel (0.125 mg/kg/day) to pregnant female rats from gestation day 16 through lactation day 20 reduced pup survival, but did not affect the reproductive capacity of the offspring. Based on data from another study, the maximum systemic exposure in the rat would be equivalent to the maximum systemic exposure in subjects treated with the MRHD of tazarotene cream, 0.1%.

8.2 Lactation

Risk Summary

There is no information regarding the presence of tazarotene in human milk, the effects on the breastfed infant, or the effects on milk production. After single topical doses of ^14C-tazarotene gel to the skin of lactating rats, radioactivity was detected in rat milk. The lack of clinical data during lactation precludes a clear determination of the risk of TAZORAC Cream to an infant during lactation; therefore, the developmental and health benefits of breastfeeding should be considered along with the mother’s clinical need for TAZORAC Cream and any potential adverse effects on the breastfed child from TAZORAC Cream or from the underlying maternal condition.

8.3 Females and Males of Reproductive Potential

Pregnancy Testing

Pregnancy testing is recommended for females of reproductive potential within 2 weeks prior to initiating TAZORAC Cream therapy which should begin during a menstrual period.

Contraception

Females

Based on animal studies, TAZORAC Cream may cause fetal harm when administered to a pregnant woman [see Use in Specific Populations (8.1)]. Advise females of reproductive potential to use effective contraception during treatment with TAZORAC Cream.

8.4 Pediatric Use

The safety and efficacy of TAZORAC Cream have not been established in patients with psoriasis under the age of 18 years, or in patients with acne under the age of 12 years.

8.5 Geriatric Use

TAZORAC Cream for the treatment of acne has not been clinically tested in persons 65 years of age or older.

Of the total number of subjects in clinical trials of TAZORAC Cream for plaque psoriasis, 120 were over the age of 65. No overall differences in safety or effectiveness were observed between these subjects and younger subjects. Currently there is no other clinical experience on the differences in responses between the elderly and younger subjects, but greater sensitivity of some older individuals cannot be ruled out.

10 OVERDOSAGE

Excessive topical use of TAZORAC Cream, 0.05% and 0.1% may lead to marked redness, peeling, or discomfort [see Warnings and Precautions (5.2)].

TAZORAC Cream, 0.05% and 0.1% are not for oral use. Oral ingestion of the drug may lead to the same adverse effects as those associated with excessive oral intake of Vitamin A (hypervitaminosis A) or other retinoids. If oral ingestion occurs, the patient should be monitored, and appropriate supportive measures should be administered as necessary.

11 DESCRIPTION

TAZORAC (tazarotene) Cream, 0.05% and 0.1% is for topical use and contains the active ingredient, tazarotene. Each gram of TAZORAC Cream, 0.05% and 0.1% contains 0.5 and 1 mg of tazarotene, respectively in a white cream base.

Tazarotene is a member of the acetylenic class of retinoids. Chemically, tazarotene is ethyl 6-[(4,4-dimethylthiochroman-6-yl) ethynyl]nicotinate. The compound has an empirical formula of C21H21NO2S and molecular weight of 351.46. The structural formula is shown below:

TAZORAC Cream contains the following inactive ingredients: benzyl alcohol 1%; carbomer 1342; carbomer homopolymer type B; edetate disodium; medium chain triglycerides; mineral oil; purified water; sodium hydroxide; sodium thiosulfate; and sorbitan monooleate.

12 CLINICAL PHARMACOLOGY

12.1 Mechanism of Action

Tazarotene is a retinoid prodrug which is converted to its active form, the carboxylic acid of tazarotene, by deesterification. Tazarotenic acid binds to all three members of the retinoic acid receptor (RAR) family: RARα, RARβ, and RARɣ, but shows relative selectivity for RARβ, and RARɣ and may modify gene expression. The clinical significance of these findings is unknown.

12.3 Pharmacokinetics

Following topical application, tazarotene undergoes esterase hydrolysis to form its active metabolite, tazarotenic acid. Little parent compound could be detected in the plasma. Tazarotenic acid was highly bound to plasma proteins (greater than 99%). Tazarotene and tazarotenic acid were metabolized to sulfoxides, sulfones and other polar metabolites which were eliminated through urinary and fecal pathways. The half-life of tazarotenic acid was approximately 18 hours, following topical application of tazarotene to normal, acne or psoriatic skin.

In a multiple dose trial with a once daily dose for 14 consecutive days in 9 psoriatic subjects (male=5; female=4), measured doses of TAZORAC Cream, 0.1% were applied by medical staff to involved skin without occlusion (5 to 35% of total body surface area: mean ± SD: 14 ± 11%). The Cmax of tazarotenic acid was 2.31 ± 2.78 ng/mL occurring 8 hours after the final dose, and the AUC0-24h was 31.2 ± 35.2 ng·hr/mL on day 15 in the five subjects who were administered clinical doses of 2 mg cream/cm^2.

During clinical trials with TAZORAC Cream, 0.05% or 0.1% treatment for plaque psoriasis, three out of 139 subjects with their systemic exposure monitored had detectable plasma tazarotene concentrations, with the highest value at 0.09 ng/mL. Tazarotenic acid was detected in 78 out of 139 subjects (LLOQ = 0.05 ng/mL). Three subjects using tazarotene cream 0.1% had plasma tazarotenic acid concentrations greater than 1 ng/mL. The highest value was 2.4 ng/mL. However, because of the variations in the time of blood sampling, the area of psoriasis involvement, and the dose of tazarotene applied, actual maximal plasma levels are unknown.

TAZORAC Cream 0.1% was applied once daily to either the face (N=8) or to 15% of body surface area (N=10) of female subjects with moderate to severe acne vulgaris. The mean Cmax and AUC values of tazarotenic acid peaked at day 15 for both dosing groups during a 29 day treatment period. Mean Cmax and AUC0-24h values of tazarotenic acid from subjects in the 15% body surface area dosing group were more than 10 times higher than those from subjects in the face-only dosing group. The single highest Cmax throughout the trial period was 1.91 ng/mL on day 15 in the exaggerated dosing group. In the face-only group, the mean ± SD values of Cmax and AUC0-24h of tazarotenic acid on day 15 were 0.10 ± 0.06 ng/mL and 1.54 ± 1.01 ng·hr/mL, respectively, whereas in the 15% body surface area dosing group, the mean ± SD values of Cmax and AUC0-24h of tazarotenic acid on day 15 were 1.20 ± 0.41 ng/mL and 17.01 ± 6.15 ng·hr/mL, respectively. The steady state pharmacokinetics of tazarotenic acid had been reached by day 8 in the face-only and by day 15 in the 15% body surface area dosing groups.

In a Phase 3 clinical trial, TAZORAC Cream, 0.1% was applied once daily for 12 weeks to each of 48 subjects (22 females and 26 males) with facial acne vulgaris. The mean ± SD values of plasma tazarotenic acid at weeks 4 and 8 were 0.078 ± 0.073 ng/mL (N=47) and 0.052 ± 0.037 ng/mL (N=42), respectively. The highest observed individual plasma tazarotenic acid concentration was 0.41 ng/mL at week 4 from a female subject. The magnitude of plasma tazarotenic acid concentrations appears to be independent of gender, age, and body weight.

13 NONCLINICAL TOXICOLOGY

13.1 Carcinogenesis, Mutagenesis, Impairment of Fertility

Carcinogenesis

A long-term study of tazarotene following oral administration of 0.025, 0.050, and 0.125 mg/kg/day to rats showed no indications of increased carcinogenic risks. Based on pharmacokinetic data from a shorter term study in rats, the highest dose of 0.125 mg/kg/day was anticipated to give systemic exposure in the rat equivalent to 0.6 times that seen in a psoriatic patient treated with 0.1% tazarotene cream at 2 mg/kg/cm^2 over a 35% body surface area in a controlled pharmacokinetic study. This estimated systemic exposure in rats was 2 times the maximum systemic exposure in acne patients treated with tazarotene cream, 0.1% cream at 2 mg/cm^2 over a 15% body surface area.

A long-term topical application study of up to 0.1% of tazarotene in a gel formulation in mice terminated at 88 weeks showed that dose levels of 0.05, 0.125, 0.25, and 1 mg/kg/day (reduced to 0.5 mg/kg/day for males after 41 weeks due to severe dermal irritation) revealed no apparent carcinogenic effects when compared to vehicle control animals. Systemic exposures at the highest dose was 3.9 times that seen in a psoriatic patient treated with 0.1% tazarotene cream at 2 mg/cm^2 over a 35% body surface area in a controlled pharmacokinetic study, and 13 times the maximum systemic exposure in acne patients treated with tazarotene cream, 0.1% at 2 mg/cm^2 over a 15% body surface area.

In evaluation of photo co-carcinogenicity, median time to onset of tumors was decreased, and the number of tumors increased in hairless mice following chronic topical dosing with intercurrent exposure to ultraviolet radiation at tazarotene concentrations of 0.001%, 0.005%, and 0.01% in a gel formulation for up to 40 weeks.

Mutagenesis

Tazarotene was found to be non-mutagenic in the Ames assay and did not produce structural chromosomal aberrations in a human lymphocyte assay. Tazarotene was non-mutagenic in the CHO/HGPRT mammalian cell forward gene mutation assay and was non-clastogenic in the in vivo mouse micronucleus test.

Impairment of Fertility

No impairment of fertility occurred in rats when male animals were treated for 70 days prior to mating and female animals were treated for 14 days prior to mating and continuing through gestation and lactation with topical doses of tazarotene gel up to 0.125 mg/kg/day. Based on data from another study, the systemic drug exposure in the rat would be equivalent to 0.6 times that observed in a psoriatic patient treated with 0.1% tazarotene cream at 2 mg/cm^2 over a 35% body surface area in a controlled pharmacokinetic study, and 2 times the maximum systemic exposure in acne patients treated with tazarotene cream, 0.1% at 2 mg/cm^2 over a 15% body surface area.

No impairment of mating performance or fertility was observed in male rats treated for 70 days prior to mating with oral doses of up to 1 mg/kg/day tazarotene. That dose produced a systemic exposure that was 1.9 times that observed in a psoriatic patient treated with 0.1% tazarotene cream at 2 mg/cm^2 over a 35% body surface area, and 6.3 times the maximum systemic exposure in acne patients treated with tazarotene cream, 0.1% at 2 mg/cm^2 over a 15% body surface area.

No impairment of mating performance or fertility was observed in female rats treated for 15 days prior to mating and continuing through gestation day 7 with oral doses up to 2 mg/kg/day of tazarotene. However, there was a significant decrease in the number of estrous stages and an increase in developmental effects at that dose [see Use in Specific Populations (8.1)]. That dose produced a systemic exposure that was 3.4 times that observed in a psoriatic patient treated with 0.1% tazarotene cream at 2 mg/cm^2 over a 35% body surface area and 11 times the maximum systemic exposure in acne patients treated with tazarotene cream, 0.1% at 2 mg/cm^2 over a 15% body surface area.

Reproductive capabilities of F1 animals, including F2 survival and development, were not affected by topical administration of tazarotene gel to female F0 parental rats from gestation day 16 through lactation day 20 at the maximum tolerated dose of 0.125 mg/kg/day. Based on data from another study, the systemic drug exposure in the rat would be equivalent to 0.6 times that observed in a psoriatic patient treated with 0.1% tazarotene cream at 2 mg/cm^2 over a 35% body surface area, and 2 times the maximum systemic exposure in acne patients treated with tazarotene cream, 0.1% at 2 mg/cm^2 over a 15% body surface area.

14 CLINICAL STUDIES

In two 12-week vehicle-controlled clinical trials, TAZORAC Cream, 0.05% and 0.1% was significantly more effective than vehicle in reducing the severity of stable plaque psoriasis. TAZORAC Cream, 0.1% and 0.05% demonstrated superiority over vehicle cream as early as 1 week and 2 weeks, respectively, after starting treatment.
In these trials, the primary efficacy endpoint was “clinical success,” defined as the proportion of subjects with none, minimal, or mild overall lesional assessment at Week 12, and shown in Table 1. “Clinical success” was also significantly greater with TAZORAC Cream, 0.05% and 0.1% versus vehicle at most follow-up visits.

Table 1. Subject Numbers and Percentages for Overall Lesional Assessment Scores and “Clinical Success” at Baseline (BL), End of Treatment (Week 12) and 12 Weeks After Stopping Therapy (Week 24)# in Two Controlled Clinical Trials for Psoriasis
 | TAZORAC Cream, 0.05% |  |  |  |  | TAZORAC Cream, 0.1% |  |  |  |  | Vehicle Cream
 | Trial 1 N=218 |  |  | Trial 2 N=210 |  | Trial 1 N=221 |  |  | Trial 2 N=211 |  | Trial 1 N=229 |  |  | Trial 2 N=214
Score | BL | Wk 12 | Wk 24 | BL | Wk 12 | BL | Wk 12 | Wk 24 | BL | Wk 12 | BL | Wk 12 | Wk 24 | BL | Wk 12
None (0) | 0 | 1 (0.5%) | 1 (0.5%) | 0 | 2 (1%) | 0 | 0 | 0 | 0 | 6 (3%) | 0 | 0 | 1 (0.4%) | 0 | 1 (0.5%)
Minimal (1) | 0 | 11 (5%) | 12 (6%) | 0 | 7 (3%) | 0 | 12 (5%) | 14 (6%) | 0 | 11 (5%) | 0 | 7 (3%) | 6 (3%) | 0 | 1 (0.5%)
Mild (2) | 0 | 79 (36%) | 60 (28%) | 0 | 76 (36%) | 0 | 75 (34%) | 53 (24%) | 0 | 90 (43%) | 0 | 49 (21%) | 43 (19%) | 0 | 54 (25%)
Moderate (3) | 141 (65%) | 86 (39%) | 90 (41%) | 100 (48%) | 74 (35%) | 122 (55%) | 97 (44%) | 107 (48%) | 96 (45%) | 62 (29%) | 139 (61%) | 119 (52%) | 114 (50%) | 97 (45%) | 99 (46%)
Severe (4) | 69 (32%) | 39 (18%) | 51 (23%) | 80 (38%) | 36 (17%) | 91 (41%) | 36 (16%) | 46 (21%) | 86 (41%) | 29 (14%) | 81 (35%) | 51 (22%) | 61 (27%) | 93 (44%) | 47 (22%)
Very Severe (5) | 8 (4%) | 2 (0.9%) | 4 (2%) | 30 (14%) | 15 (7%) | 8 (4%) | 1 (0.5%) | 1 (0.5%) | 29 (14%) | 13 (6%) | 9 (4%) | 3 (1%) | 4 (2%) | 24 (11%) | 12 (6%)
“Clinical Success” | 0 | 91 (42%*) | 73 (33%*) | 0 | 85 (40%*) | 0 | 87 (39%*) | 67 (30%*) | 0 | 107 (51%*) | 0 | 56 (24%) | 50 (22%) | 0 | 56 (26%)
0 no plaque elevation above normal skin level; may have residual non-erythematous discoloration; no psoriatic scale
1 essentially flat with possible trace elevation; may have up to moderate erythema (red coloration); no psoriatic scale
2 slight but definite elevation of plaque above normal skin level; may have up to moderate erythema (red coloration); fine scales with some lesions partially covered
3 moderate elevation with rounded or sloped edges to plaque; moderate erythema (red coloration); somewhat coarser scales with most lesions partially covered
4 marked elevation with hard, sharp edges to plaque; severe erythema (very red coloration); thick scales with virtually all lesions covered and a rough surface
5 very marked elevation with very hard, sharp edges to plaque; very severe erythema (extreme red coloration); very coarse, thick scales with all lesions covered and a very rough surface
Clinical Success defined as an overall lesional assessment score of none, minimal, or mild.
# Trial 1 had post-treatment period observations for 12 weeks after stopping therapy, which were not part of Trial 2.
* Denotes statistically significant difference for “Clinical Success” compared with vehicle.

At the end of 12 weeks of treatment, TAZORAC Cream, 0.05% and 0.1% was consistently superior to vehicle in reducing the plaque thickness of psoriasis. Improvements in erythema and scaling were generally significantly greater with TAZORAC Cream, 0.05% and 0.1% than with vehicle. TAZORAC Cream, 0.1% was also generally more effective than TAZORAC Cream, 0.05% in reducing the severity of the individual signs of disease. However, TAZORAC Cream, 0.1% was associated with a greater degree of local irritation than TAZORAC Cream, 0.05%.

Table 2. Mean Decreases in Plaque Elevation, Scaling and Erythema in Two Controlled Clinical Trials for Psoriasis
 |  | TAZORAC Cream, 0.05% |  |  |  |  |  | TAZORAC Cream, 0.1% |  |  |  |  |  | Vehicle Cream
Lesion |  | Trunk/Arm/ Leg lesions |  | Knee/Elbow lesions |  | All Treated |  | Trunk/Arm/ Leg lesions |  | Knee/Elbow lesions |  | All Treated |  | Trunk/Arm/ Leg lesions |  | Knee/Elbow lesions |  | All Treated
 |  | Trial 1 | Trial 2 | Trial 1 | Trial 2 | Trial 1 | Trial 2 | Trial 1 | Trial 2 | Trial 1 | Trial 2 | Trial 1 | Trial 2 | Trial 1 | Trial 2 | Trial 1 | Trial 2 | Trial 1 | Trial 2
 |  | N=218 | N=210 | N=218 | N=210 | N=218 | N=210 | N=221 | N=211 | N=221 | N=211 | N=221 | N=211 | N=229 | N=214 | N=229 | N=214 | N=229 | N=214
Plaque elevation | B# C-12 C-24 | 2.29 -0.83* -0.75* | 2.50 -0.98* | 2.40 -0.91* -0.73* | 2.52 -1.04* | 2.28 -0.75* -0.60* | 2.51 -0.90* | 2.34 -1.08* -0.87* | 2.52 -1.25* | 2.35 -0.96* -0.73* | 2.49 -1.21* | 2.32 -0.83* -0.63* | 2.51 -1.08* | 2.28 -0.59 -0.57 | 2.51 -0.69 | 2.35 -0.57 -0.49 | 2.51 -0.68 | 2.29 -0.48 -0.42 | 2.51 -0.61
Scaling | B# C-12 C-24 | 2.26 -0.75 -0.68 | 2.45 -0.90 | 2.47 -0.78* -0.62* | 2.60 -0.98* | 2.32 -0.67* -0.51* | 2.47 -0.80 | 2.37 -0.84* -0.79* | 2.45 -1.06* | 2.40 -0.76* -0.61* | 2.57 -1.13* | 2.36 -0.73* -0.59* | 2.53 -1.03* | 2.34 -0.66 -0.56 | 2.46 -0.79 | 2.45 -0.62 -0.45 | 2.61 -0.76 | 2.31 -0.46 -0.34 | 2.53 -0.70
Erythema | B# C-12 C-24 | 2.26 -0.49 -0.52 | 2.51 -0.65* | 2.17 -0.44 -0.44 | 2.40 -0.66* | 2.23 -0.40 -0.41 | 2.48 -0.62 | 2.25 -0.49 -0.55 | 2.53 -0.82* | 2.17 -0.57* -0.52* | 2.42 -0.82* | 2.21 -0.42* -0.39* | 2.51 -0.78* | 2.24 -0.42 -0.43 | 2.47 -0.46 | 2.17 -0.38 -0.34 | 2.34 -0.44 | 2.24 -0.37 -0.33 | 2.47 -0.47
Plaque elevation, scaling and erythema scored on a 0-4 scale with 0=none, 1=mild, 2=moderate, 3=severe and 4=very severe.
B#=Mean Baseline Severity;
C-12=Mean Change from Baseline at end of 12 weeks of therapy;
C-24=Mean Change from Baseline at week 24 (12 weeks after the end of therapy).
*Denotes statistically significant difference compared with vehicle.

Acne:

In two large vehicle-controlled trials, subjects age 12 years and over with facial acne vulgaris of a severity suitable for monotherapy with a topical agent were enrolled. After face cleansing in the evening, TAZORAC Cream, 0.1% was applied once daily to the entire face as a thin layer. TAZORAC Cream, 0.1% was significantly more effective than vehicle in the treatment of facial acne vulgaris. Efficacy results after 12 weeks of treatment are shown in Table 3:

Table 3. Efficacy Results after Twelve Weeks of Treatment in Two Controlled Clinical Trials for Acne
 | TAZORAC Cream, 0.1% |  | Vehicle Cream
 | Trial 1 N=218 | Trial 2 N=206 | Trial 1 N=218 | Trial 2 N=205
Median Percent Reduction in
- Noninflammatory lesions | 46%* | 41%* | 27% | 21%
- Inflammatory lesions | 41%* | 44%* | 27% | 25%
- Total lesions | 44%* | 42%* | 24% | 21%
Percent of Subjects with No Acne or Minimal Acne | 18%* | 20%* | 11% | 6%
Percent of Subjects with No Acne, Minimal Acne, or Mild Acne | 55%* | 53%* | 36% | 36%
*Denotes statistically significant difference compared with vehicle.

16 HOW SUPPLIED/STORAGE AND HANDLING

TAZORAC Cream is a white cream available in concentrations of 0.05% and 0.1%. It is supplied in a collapsible aluminum tube with a tamper-evident aluminum membrane over the opening and a white polypropylene screw cap, in 30 g and 60 g sizes.

 | TAZORAC Cream, 0.05% | TAZORAC Cream, 0.1%
30 g | NDC 16110-915-30 | NDC 16110-916-30
60 g | NDC 16110-915-60 | NDC 16110-916-60

STORAGE AND HANDLING

Storage: Store at 20°C to 25°C (68°F to 77°F). Excursions permitted from -5°C to 30°C (23°F to 86°F).

17 PATIENT COUNSELING INFORMATION

Advise the patient to read the FDA-approved patient labeling (Patient Information).

Embryofetal Toxicity

Inform females of reproductive potential of the potential risk to a fetus. Advise these patients to use effective contraception during treatment with TAZORAC Cream. Advise patients to inform their healthcare provider of a known or suspected pregnancy [see Warnings and Precautions (5.1) and Use in Specific Populations (8.1, 8.3)].

Photosensitivity and Risk of Sunburn

Advise patients to avoid excessive sun exposure and to use of sunscreens and protective measures (hat, visor). Advise patients to avoid using TAZORAC if also taking other medicines may increase sensitivity to sunlight.

Important Administration Instructions

Advise the patient of the following:

1. For the patient with psoriasis, apply TAZORAC Cream only to psoriasis skin lesions, avoiding uninvolved skin.
2. If undue irritation (redness, peeling, or discomfort) occurs, reduce frequency of application or temporarily interrupt treatment. Treatment may be resumed once irritation subsides [see Dosage and Adminstration (2.1)].
3. Moisturizers may be used as frequently as desired.
4. Patients with psoriasis may use a cream or lotion to soften or moisten skin at least 1 hour before applying TAZORAC Cream.
5. Avoid contact with the eyes. If TAZORAC Cream gets in or near eyes, rinse thoroughly with water. Seek medical attention if eye irritation continues.
6. TAZORAC Cream is for topical use only. Do not apply to eyes, mouth, or other mucous membrane. Not for ophthalmic, oral, or intravaginal use.
7. Wash hands thoroughly after applying TAZORAC Cream.

Distributed by Almirall, LLC
Exton, PA 19341

© 2019 Almirall, Inc. All rights reserved.
All trademarks are the property of their respective owners.

72709AM11

PATIENT INFORMATION
TAZORAC® (TAZ-or-ac)
(tazarotene)
Cream, 0.05% and 0.1%

Important information: TAZORAC Cream is for use on skin only. Do not use TAZORAC Cream in your eyes, mouth, or vagina.

What is the most important information I should know about TAZORAC Cream?
TAZORAC Cream may cause birth defects if used during pregnancy.

- Females must not be pregnant when they start using TAZORAC Cream or become pregnant during treatment with TAZORAC Cream.
- For females who are able to get pregnant:
  - Your doctor will order a pregnancy test for you within 2 weeks before you begin treatment with TAZORAC Cream to be sure that you are not pregnant. Your doctor will decide when to do the test.
  - Begin treatment with TAZORAC Cream during a normal menstrual period.
  - Use an effective form of birth control during treatment with TAZORAC Cream. Talk with your doctor about birth control options that may be used to prevent pregnancy during treatment with TAZORAC Cream.
  - Stop using TAZORAC Cream and tell your doctor right away if you become pregnant while using TAZORAC Cream.

What is TAZORAC Cream?

- TAZORAC Cream 0.05% and 0.1% is a prescription medicine used on the skin (topical) to treat people with plaque psoriasis.
- TAZORAC Cream 0.1% is also used on the skin to treat people with acne vulgaris.
- It is not known if TAZORAC Cream is safe and effective for:
  - the treatment of plaque psoriasis in children under 18 years of age
  - the treatment of acne vulgaris in children under 12 years of age

Who should not use TAZORAC Cream?
Do not use TAZORAC Cream if you:

- are pregnant or plan to become pregnant. See “What is the most important information I should know about TAZORAC Cream?” at the beginning of this leaflet.
- are allergic to tazarotene or any of the ingredients in TAZORAC Cream. See the end of this leaflet for a complete list of ingredients in TAZORAC Cream.

What should I tell my doctor before using TAZORAC Cream?
Before you use TAZORAC Cream, tell your doctor about all of your medical conditions, including if you:

- have eczema or any other skin problems
- are breastfeeding or plan to breastfeed. It is not known if TAZORAC Cream passes into your breast milk. Talk to your doctor about using TAZORAC Cream while breastfeeding.

Tell your doctor about all the medicines you take, including prescription and over-the-counter medicines, vitamins, and herbal supplements.
Certain medicines, vitamins, or supplements may make your skin more sensitive to sunlight.
Also, tell your doctor about any cosmetics you use, including moisturizers, creams, lotions, or products that can dry out your skin.

How should I use TAZORAC Cream?

- Use TAZORAC Cream exactly as your doctor tells you to use it.
- Apply TAZORAC Cream 1 time each day, in the evening.
- Do not get TAZORAC Cream in your eyes, on your eyelids, or in your mouth. If TAZORAC Cream gets in or near your eyes, rinse them well with water. Call your doctor or get medical help if you have eye irritation that does not go away.
- Wash your hands after applying TAZORAC Cream.

Follow these instructions for applying TAZORAC Cream:

- If you have psoriasis:
  - If you shower or bathe before applying TAZORAC Cream, your skin should be dry before applying the cream.
  - You may use a cream or lotion to soften or moisten your skin at least 1 hour before you apply TAZORAC Cream.
  - Apply a thin layer of TAZORAC Cream to cover only the psoriasis lesions.
- If you have acne:
  - Gently wash and dry your face before applying TAZORAC Cream.
  - Apply a thin layer of TAZORAC Cream to cover only the acne lesions.
- If you swallow TAZORAC Cream, call your doctor or go to the nearest hospital emergency room right away.

What should I avoid while using TAZORAC Cream?

- Avoid sunlight, including sunlamps, during treatment with TAZORAC Cream. TAZORAC Cream can make you more sensitive to the sun, and the light from sunlamps and tanning beds. You could get a severe sunburn. Use sunscreen and wear a hat and clothes that cover your skin if you have to be in sunlight.
- Talk to your doctor if you get a sunburn during treatment with TAZORAC Cream. If you get a sunburn, do not use TAZORAC Cream until your sunburn is healed.
- Avoid using cosmetics or topical medicines that may make your skin more sensitive to sunlight or make your skin dry.
- Avoid using TAZORAC Cream on unaffected skin or skin with eczema because it may cause severe irritation.

What are the possible side effects of TAZORAC Cream?
TAZORAC Cream may cause serious side effects, including:

- Skin irritation and allergic reactions (hypersensitivity). TAZORAC Cream may cause increased skin irritation and hives. Tell your doctor if you develop hives, or itching, burning, redness, or peeling of your skin during treatment with TAZORAC Cream. If you develop hives or skin irritation, your doctor may tell you to stop using TAZORAC Cream until your skin heals, tell you to use TAZORAC Cream less often, or change your TAZORAC Cream dose. Also, wind or cold weather may be more irritating to your skin while you are using TAZORAC Cream.
- Sensitivity to sunlight and risk of sunburn. See “What should I avoid while using TAZORAC Cream?”

The most common side effects of TAZORAC Cream in people with psoriasis include itching, redness and burning.
The most common side effects of TAZORAC Cream in people with acne include peeling, dry skin, redness and burning.
These are not all the possible side effects of TAZORAC Cream. Call your doctor for medical advice about side effects. You may report side effects to FDA at 1-800-FDA-1088.

How should I store TAZORAC Cream?

- Store TAZORAC Cream at room temperature between 68°F to 77°F (20°C to 25°C).
- Keep TAZORAC Cream and all medicines out of the reach of children.

General information about the safe and effective use of TAZORAC Cream.
Medicines are sometimes prescribed for purposes other than those listed in a Patient Information leaflet. Do not use TAZORAC Cream for a condition for which it was not prescribed. Do not give TAZORAC Cream to other people, even if they have the same symptoms you have. It may harm them. You can ask your doctor or pharmacist for information about TAZORAC Cream that is written for health professionals.

What are the ingredients in TAZORAC Cream?
Active ingredient: tazarotene
Inactive ingredients: benzyl alcohol 1%, carbomer 1342, carbomer homopolymer type B, edetate disodium, medium chain triglycerides, mineral oil, purified water, sodium hydroxide, sodium thiosulfate, and sorbitan monooleate

Distributed by: Almirall, LLC, Exton, PA 19341

© 2019 Almirall, Inc. All rights reserved.

almirall

All trademarks are the property of their respective owners.

For more information call 1-800-678-1605 or go to www.tazorac.com.

This Patient Information has been approved by the U.S. Food and Drug Administration

Revised: August 2019

72709AM11